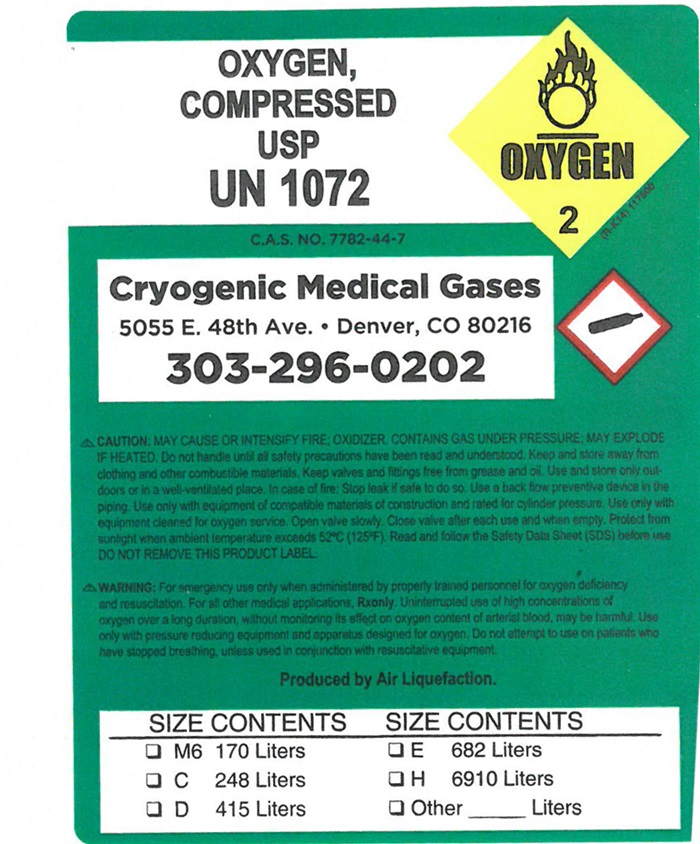 DRUG LABEL: Oxygen
NDC: 62504-968 | Form: GAS
Manufacturer: Cryogenic Medical Gases, LLC
Category: prescription | Type: HUMAN PRESCRIPTION DRUG LABEL
Date: 20180303

ACTIVE INGREDIENTS: Oxygen 99 L/100 L

Oxygen

PACKAGE LABEL

UN1073

OXYGEN, REFRIGERATED LIQUID USP

↑ALWAYS KEEP CONTAINER IN UPRIGHT POSITION↑

DO NOT CHANGE OR FORCE-FIT CONNECTIONS

LOT NUMBER ___________

NET CONTENTS _________

DANGER!

MAY CAUSE OR INTENSIFY FIRE;
OXIDIZER

CONTAINS REFIGERATED GAS; MAY CAUSE CRYOGENIC BURNS OR INJURY.
COMBUSTIBLES IN CONTACT WITH LIQUID OXYGEN MAY EXPLODE ON IGNITION OR IMPACT.

IN CASE OF EMERGENCY: CALL 1-800-645-4633

CAS: 7782-44-7

Do not habdle until all safety precautions have been read and understood. Keep and store away from clothing and other combustible materials. Keep valves and fittings free from grease and oil. Use and store only outdoors or in a well-ventilated place. Wear cold insulating gloves/face shield/eye protection. In case of fire: Stop leak if safe to do so. Use a back flow preventive device in the piping. Use only with equipment of compatible materials of construction and rated for cylinder pressure. Use only with equipment cleaned for oxygen service DO NOT change or force fit connections. Avoid spills. Do not walk on or roll equipment over spills. Close valve after each use and when empty. Always keep container in an upright position. Read and follow the Safety Data Sheet (SDS) before use. FIRST AID: IF ON SKIN: Thaw frosted parts with lukewarm water. Do not rub affected area. Get immediate medical attention.

WARNING: For emergency use only when administered by properly trained personnel for oxygen deficiency and resuscitation. For all other medical applications, Rx ONLY. Uninterrupted use of high concentrations of oxygen over a long duration, without monitoring its effects on oxygen content of arterial blood, may be harmful. Use only with pressure reducing equipment and apparatus designed for oxygen. Do not attempt to use on patients who have stopped breathing unless used in conjunction with resuscitative equipment.

PRODUCED BY AIR LIQUEFACTION

Medipure™
Medical gases

PRAXAIR

PMG-8 (8/16)

MADE IN USA

DO NOT REMOVE THIS PRODUCT LABEL

DISTRIBUTED BY PRAXAIR DISTRIBUTION, INC.
DANBURY, CT 06810-6268